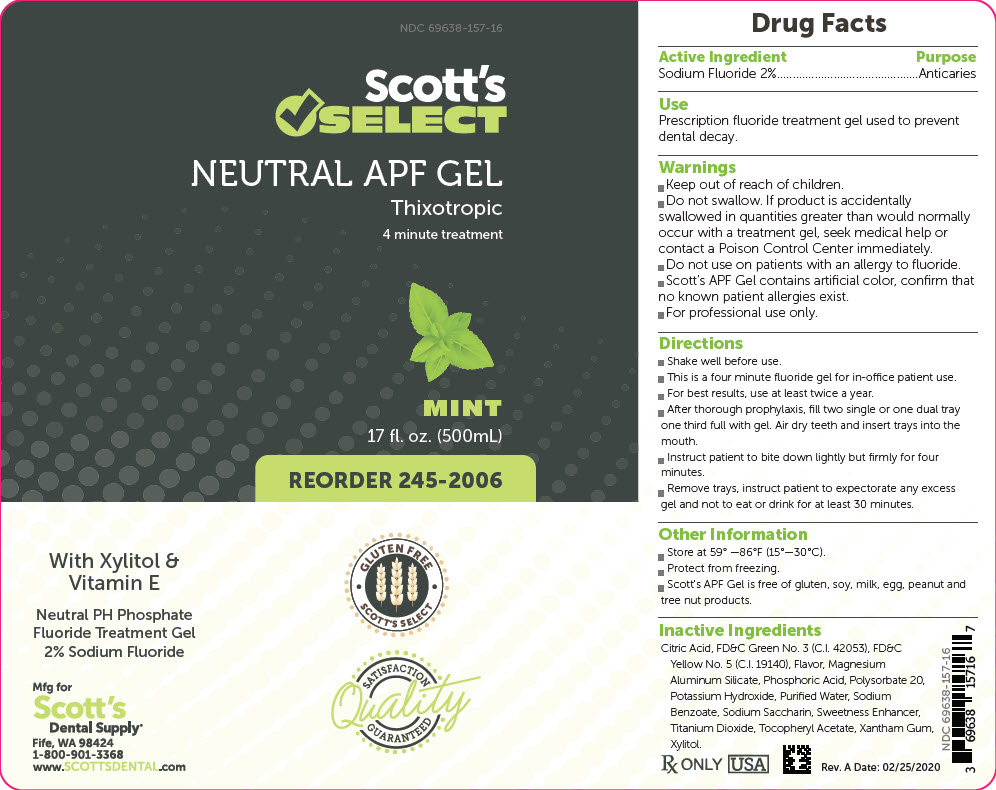 DRUG LABEL: Scotts Select Neutral APF Fluoride
NDC: 69638-157 | Form: GEL
Manufacturer: Scott's Dental Supply LLC
Category: prescription | Type: HUMAN PRESCRIPTION DRUG LABEL
Date: 20200312

ACTIVE INGREDIENTS: SODIUM FLUORIDE 0.02 g/1 mL
INACTIVE INGREDIENTS: ANHYDROUS CITRIC ACID; HYDROFLUORIC ACID; MAGNESIUM ALUMINUM SILICATE; PHOSPHORIC ACID; POLYSORBATE 20; POTASSIUM HYDROXIDE; WATER; SODIUM BENZOATE; SACCHARIN SODIUM; TITANIUM DIOXIDE; .ALPHA.-TOCOPHEROL ACETATE, DL-; XANTHAN GUM; XYLITOL; FD&C GREEN NO. 3; FD&C YELLOW NO. 5

Scott's
SELECT
NEUTRAL APF GEL

Drug Facts

Active Ingredient | Purpose
Sodium Fluoride 2% | Anticaries

Use

Prescription fluoride treatment gel used to prevent dental decay.

Warnings

- Keep out of reach of children.
- Do not swallow. If product is accidentally swallowed in quantities greater than would normally occur with a treatment gel, seek medical help or contact a Poison Control Center immediately.
- Do not use on patients with an allergy to fluoride.
- Scott's APF Gel contains artificial color, confirm that no known patient allergies exist.
- For professional use only.

Directions

- Shake well before use.
- This is a four minute fluoride gel for in-office patient use.
- For best results, use at least twice a year.
- After thorough prophylaxis, fill two single or one dual tray one third full with gel. Air dry teeth and insert trays into the mouth.
- Instruct patient to bite down lightly but firmly for four minutes.
- Remove trays, instruct patient to expectorate any excess gel and not to eat or drink for at least 30 minutes.

Other Information

- Store at 59° –86°F (15°–30°C).
- Protect from freezing.
- Scott's APF Gel is free of gluten, soy, milk, egg, peanut and tree nut products.

Inactive Ingredients

Citric Acid, FD&C Green No. 3 (C.I. 42053), FD&C Yellow No. 5 (C.I. 19140), Flavor, Magnesium Aluminum Silicate, Phosphoric Acid, Polysorbate 20, Potassium Hydroxide, Purified Water, Sodium Benzoate, Sodium Saccharin, Sweetness Enhancer, Titanium Dioxide, Tocopheryl Acetate, Xantham Gum, Xylitol.

With Xylitol & Vitamin E

Neutral PH Phosphate Fluoride Treatment Gel 2% Sodium Fluoride

Mfg for
Scott's
Dental Supply®
Fife, WA 98424
1-800-901-3368
www.SCOTTSDENTAL.com

Rx ONLY
USA
Rev. A Date: 02/25/2020

PRINCIPAL DISPLAY PANEL - 500 mL Bottle Label

NDC 69638-157-16

Scott's
✓SELECT

NEUTRAL APF GEL
Thixotropic
4 minute treatment

MINT
17 fl. oz. (500mL)

REORDER 245-2006

GLUTEN FREE
SCOTT'S SELECT

SATISFACTION
Quality
GUARANTEED